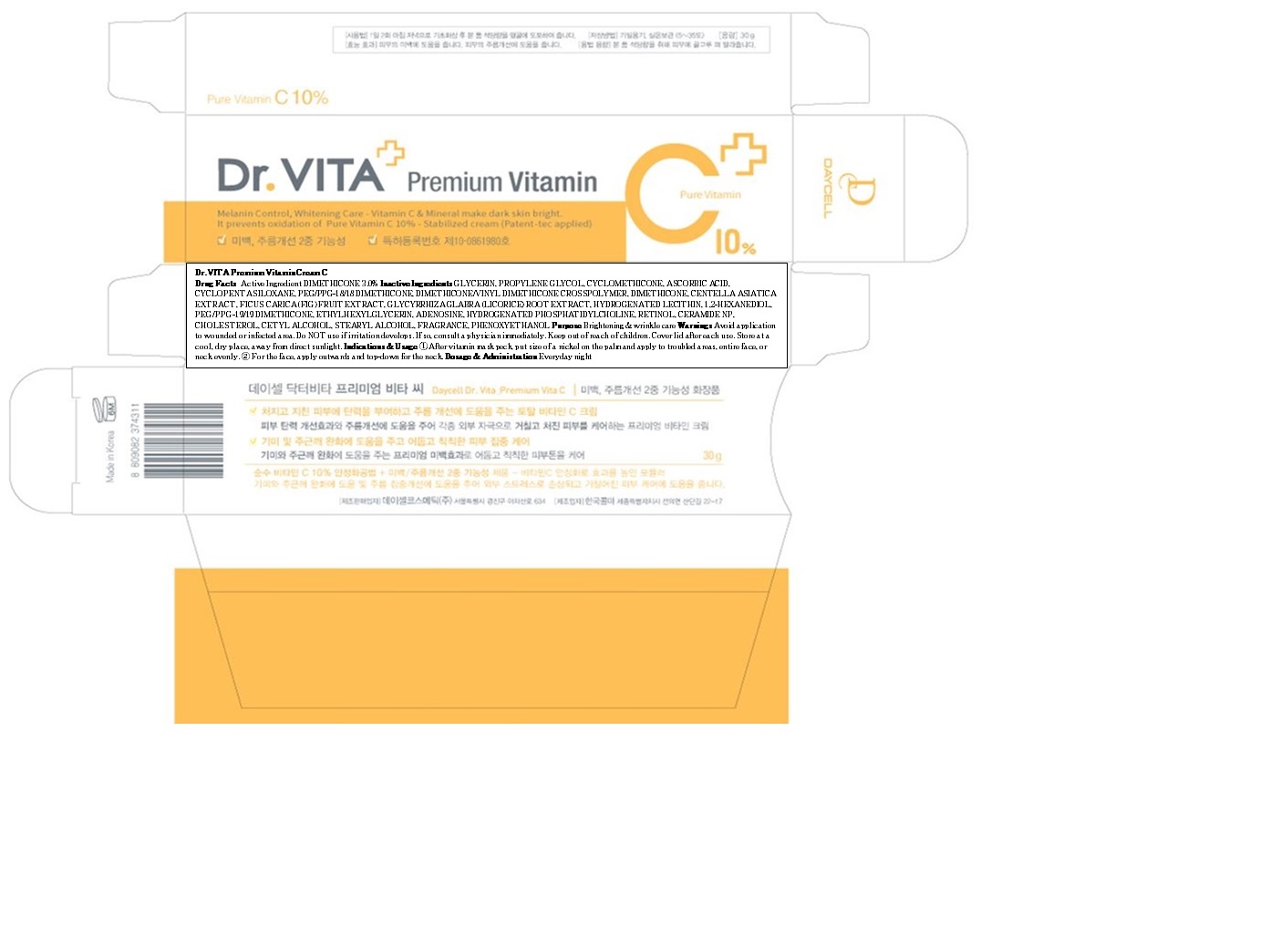 DRUG LABEL: Dr VITA Premium Vitamin C
NDC: 70545-020 | Form: CREAM
Manufacturer: DAYCELL COSMETICS CO., LTD.
Category: otc | Type: HUMAN OTC DRUG LABEL
Date: 20160328

ACTIVE INGREDIENTS: DIMETHICONE 0.9 g/30 g
INACTIVE INGREDIENTS: GLYCERIN; PROPYLENE GLYCOL

ACTIVE INGREDIENT

Active Ingredient: DIMETHICONE 3.0%

INACTIVE INGREDIENT

Inactive Ingredients: GLYCERIN, PROPYLENE GLYCOL, CYCLOMETHICONE, ASCORBIC ACID, CYCLOPENTASILOXANE, PEG/PPG-18/18 DIMETHICONE, DIMETHICONE/VINYL DIMETHICONE CROSSPOLYMER, DIMETHICONE, CENTELLA ASIATICA EXTRACT, FICUS CARICA (FIG) FRUIT EXTRACT, GLYCYRRHIZA GLABRA (LICORICE) ROOT EXTRACT, HYDROGENATED LECITHIN, 1,2-HEXANEDIOL, PEG/PPG-19/19 DIMETHICONE, ETHYLHEXYLGLYCERIN, ADENOSINE, HYDROGENATED PHOSPHATIDYLCHOLINE, RETINOL, CERAMIDE NP, CHOLESTEROL, CETYL ALCOHOL, STEARYL ALCOHOL, FRAGRANCE, PHENOXYETHANOL

PURPOSE

Purpose: Brightening & wrinkle care

WARNINGS

Warnings: Avoid application to wounded or infected area. Do NOT use if irritation develops. If so, consult a physician immediately. Keep out of reach of children. Cover lid after each use. Store at a cool, dry place, away from direct sunlight.

KEEP OUT OF REACH OF CHILDREN

INDICATIONS & USAGE

Indications & Usage: 1. After vitamin mask pack, put size of a nickel on the palm and apply to troubled areas, entire face, or neck evenly. 2. For the face, apply outwards and top-down for the neck.

DOSAGE & ADMINISTRATION

Dosage & Administration: Everyday night